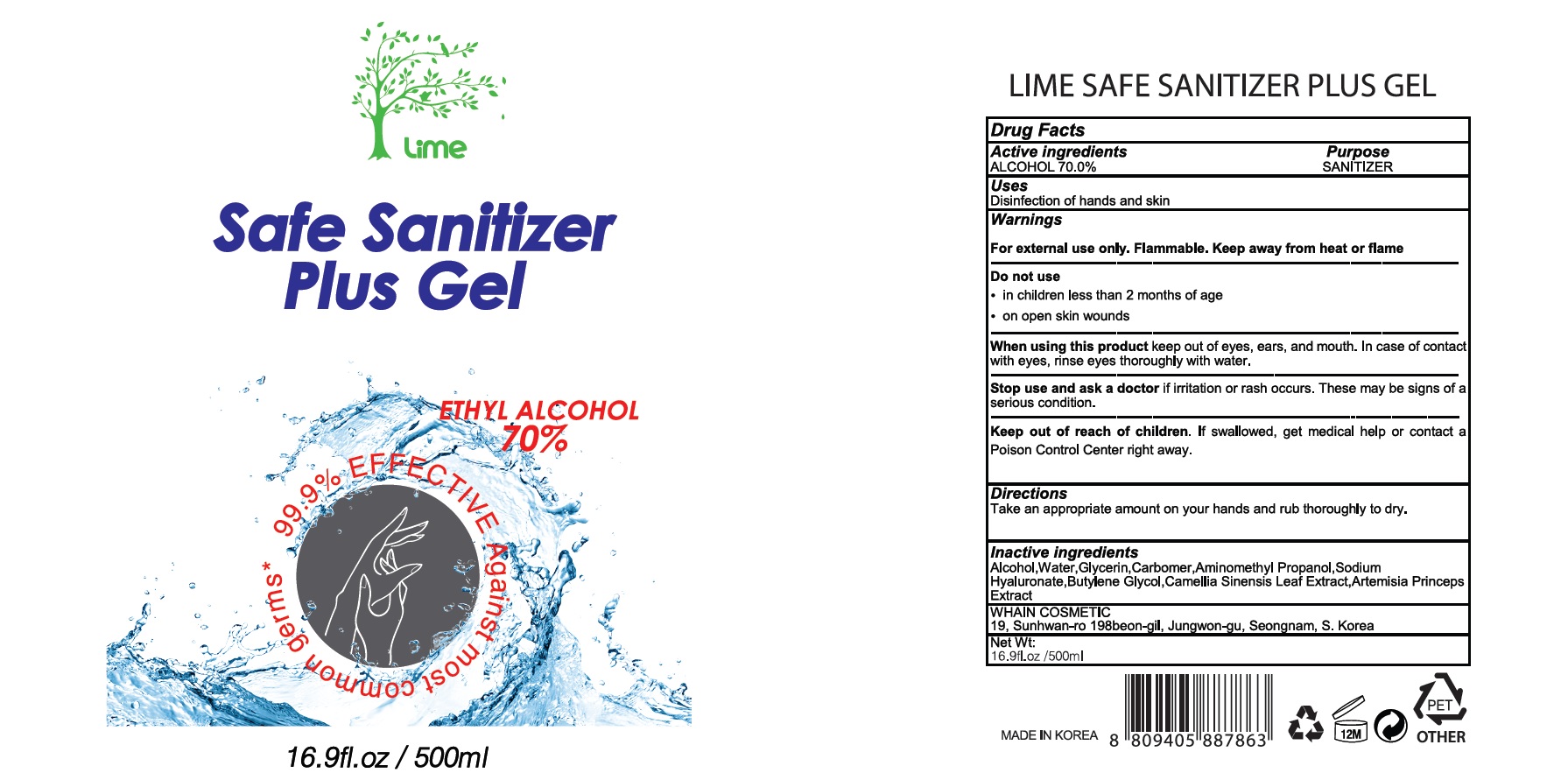 DRUG LABEL: LIME SAFE SANITIZER PLUS
NDC: 73823-070 | Form: GEL
Manufacturer: WHAIN COSMETIC
Category: otc | Type: HUMAN OTC DRUG LABEL
Date: 20200422

ACTIVE INGREDIENTS: ALCOHOL 350 mL/500 mL
INACTIVE INGREDIENTS: Water; Glycerin; CARBOMER HOMOPOLYMER, UNSPECIFIED TYPE; AMINOMETHYLPROPANOL; HYALURONATE SODIUM; Butylene Glycol; GREEN TEA LEAF

Active Ingredients

Active ingredients: ALCOHOL 70.0%

INACTIVE INGREDIENT

Inactive ingredients:

Water,Glycerin,Carbomer,Aminomethyl Propanol,Sodium Hyaluronate,Butylene Glycol,Camellia Sinensis Leaf Extract,Artemisia Princeps Extract

Purpose

Purpose: SANITIZER

Warnings

For external use only. Flammable. Keep away from heat or flame

--------------------------------------------------------------------------------------------------------
Do not use
• in children less than 2 months of age
• on open skin wounds
--------------------------------------------------------------------------------------------------------
When using this product keep out of eyes, ears, and mouth. In case of contact with eyes, rinse eyes thoroughly with water.
--------------------------------------------------------------------------------------------------------
Stop use and ask a doctor if irritation or rash occurs. These may be signs of a serious condition.
--------------------------------------------------------------------------------------------------------
Keep out of reach of children. If swallowed, get medical help or contact a Poison Control Center right away.

Keep out of reach of children. If swallowed, get medical help or contact a Poison Control Center right away.

Uses

Disinfection of hands and skin

Directions

Take an appropriate amount on your hands and rub thoroughly to dry.